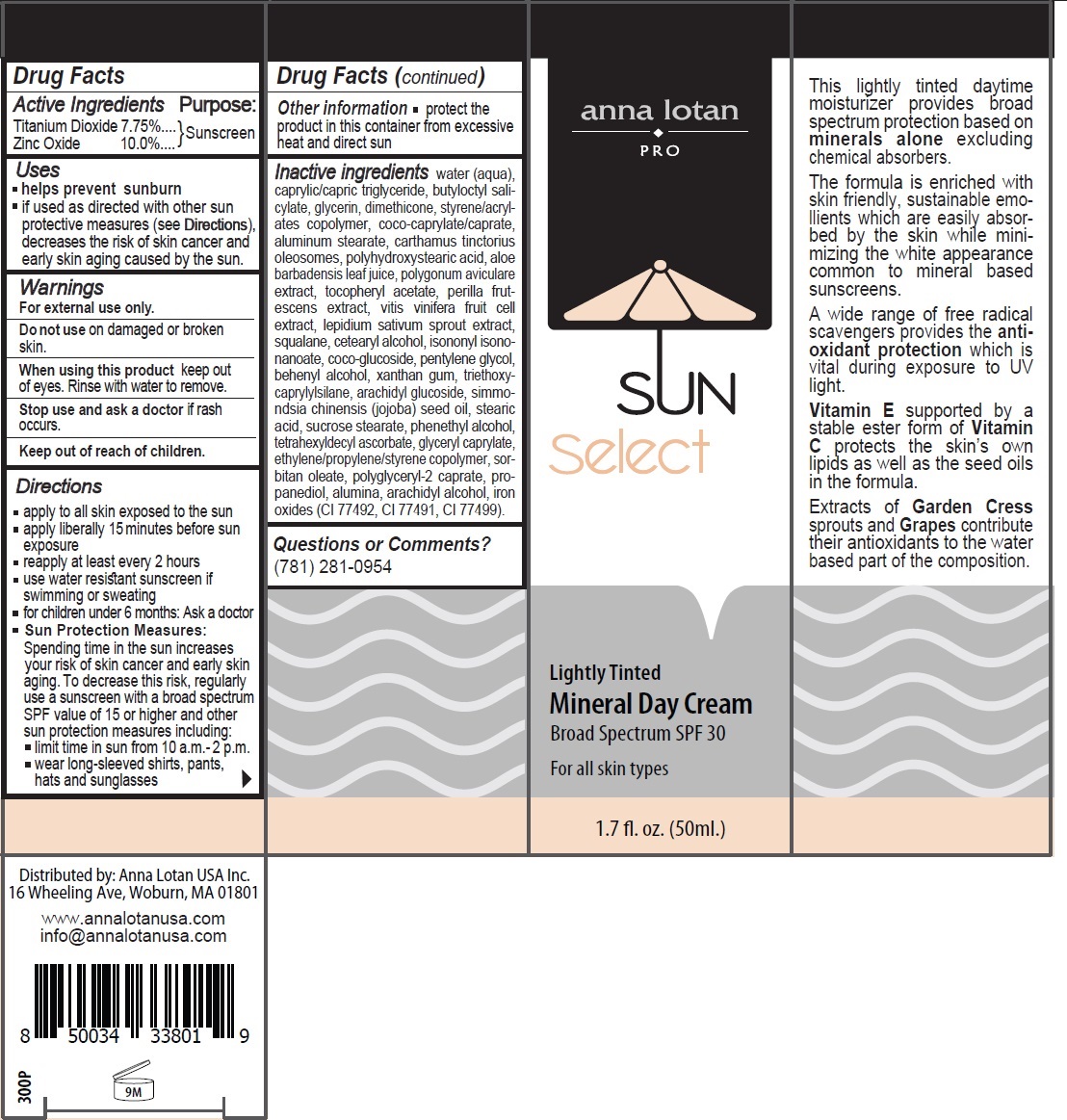 DRUG LABEL: Anna Lotan Lightly Tinted Mineral Day Cream Broad Spectrum SPF 30
NDC: 76446-300 | Form: CREAM
Manufacturer: Anna Lotan Ltd
Category: otc | Type: HUMAN OTC DRUG LABEL
Date: 20241004

ACTIVE INGREDIENTS: TITANIUM DIOXIDE 7.75 g/100 mL; ZINC OXIDE 10 g/100 mL
INACTIVE INGREDIENTS: WATER; MEDIUM-CHAIN TRIGLYCERIDES; BUTYLOCTYL SALICYLATE; GLYCERIN; DIMETHICONE; STYRENE/ACRYLAMIDE COPOLYMER (500000 MW); COCOYL CAPRYLOCAPRATE; ALUMINUM STEARATE; CARTHAMUS TINCTORIUS SEED OLEOSOMES; POLYHYDROXYSTEARIC ACID (2300 MW); ALOE VERA LEAF; POLYGONUM AVICULARE TOP; .ALPHA.-TOCOPHEROL ACETATE; PERILLA FRUTESCENS LEAF; VITIS VINIFERA HIGH TANNIN CULTIVAR FRUIT CELL LYSATE; GARDEN CRESS SPROUT; SQUALANE; CETOSTEARYL ALCOHOL; ISONONYL ISONONANOATE; COCO GLUCOSIDE; PENTYLENE GLYCOL; DOCOSANOL; XANTHAN GUM; TRIETHOXYCAPRYLYLSILANE; ARACHIDYL GLUCOSIDE; JOJOBA OIL; STEARIC ACID; SUCROSE STEARATE; PHENYLETHYL ALCOHOL; TETRAHEXYLDECYL ASCORBATE; GLYCERYL MONOCAPRYLATE; SORBITAN MONOOLEATE; POLYGLYCERYL-2 CAPRATE; PROPANEDIOL; ALUMINUM OXIDE; ARACHIDYL ALCOHOL; FERRIC OXIDE YELLOW; FERRIC OXIDE RED; FERROSOFERRIC OXIDE

anna lotan PRO SUN Select Lightly Tinted Mineral Day Cream Broad Spectrum SPF 30

Active Ingredients

Titanium Dioxide 7.75%
Zinc Oxide 10.0%

Purpose:

Sunscreen

Uses

• helps prevent sunburn
• if used as directed with other sun protective measures (see Directions), decreases the risk of skin cancer and early skin aging caused by the sun.

Warnings

For external use only.

Do not use on damaged or broken skin.

When using this product keep out of eyes. Rinse with water to remove.

Stop use and ask a doctor if rash occurs.

Keep out of reach of children.

Directions

• apply to all skin exposed to the sun
• apply liberally 15 minutes before sun exposure
• reapply at least every 2 hours
• use water resistant sunscreen if swimming or sweating
• for children under 6 months: Ask a doctor
• Sun Protection Measures:
Spending time in the sun increases your risk of skin cancer and early skin aging. To decrease this risk, regularly use a sunscreen with a broad spectrum SPF value of 15 or higher and other sun protection measures including:
• limit time in sun from 10 a.m.- 2 p.m.
• wear long-sleeved shirts, pants, hats and sunglasses

Other information

• protect the product in this container from excessive heat and direct sun

Inactive ingredients

water (aqua), caprylic/capric triglyceride, butyloctyl salicylate, glycerin, dimethicone, styrene/acrylates copolymer, coco-caprylate/caprate, aluminum stearate, carthamus tinctorius oleosomes, polyhydroxystearic acid, aloe barbadensis leaf juice, polygonum aviculare extract, tocopheryl acetate, perilla frutescens extract, vitis vinifera fruit cell extract, lepidium sativum sprout extract, squalane, cetearyl alcohol, isononyl isononanoate, coco-glucoside, pentylene glycol, behenyl alcohol, xanthan gum, triethoxycaprylylsilane, arachidyl glucoside, simmondsia chinensis (jojoba) seed oil, stearic acid, sucrose stearate, phenethyl alcohol, tetrahexyldecyl ascorbate, glyceryl caprylate, ethylene/propylene/styrene copolymer, sorbitan oleate, polyglyceryl-2 caprate, propanediol, alumina, arachidyl alcohol, iron oxides (CI 77492, CI 77491, CI 77499).

Questions or Comments?

(781) 281-0954

For all skin types

This lightly tinted daytime moisturizer provides broad spectrum protection based on minerals alone excluding chemical absorbers.

The formula is enriched with skin friendly, sustainable emollients which are easily absorbed by the skin while minimizing the white appearance common to mineral based sunscreens.

A wide range of free radical scavengers provides the antioxidant protection which is vital during exposure to UV light.

Vitamin E supported by a stable ester form of Vitamin C protects the skin’s own lipids as well as the seed oils in the formula.

Extracts of Garden Cress sprouts and Grapes contribute their antioxidants to the water based part of the composition.

Distributed by: Anna Lotan USA Inc.
16 Wheeling Ave, Woburn, MA 01801

www.annalotanusa.com
info@annalotanusa.com